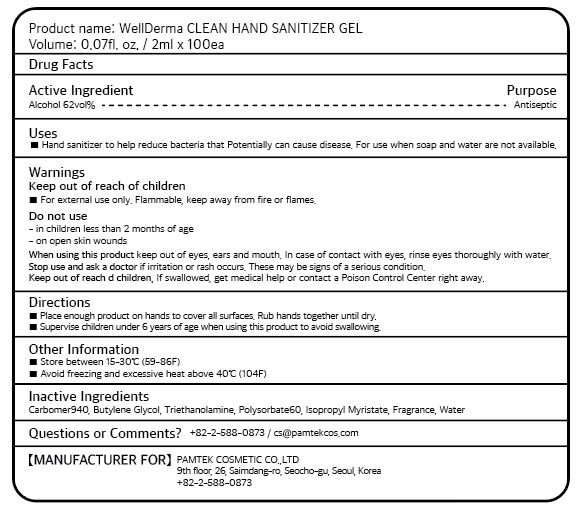 DRUG LABEL: WellDerma CLEAN HAND SANITIZER Gel
NDC: 74999-0001 | Form: GEL
Manufacturer: PPU CO., LTD
Category: otc | Type: HUMAN OTC DRUG LABEL
Date: 20210103

ACTIVE INGREDIENTS: ALCOHOL 1.24 mL/2 mL
INACTIVE INGREDIENTS: POLYSORBATE 60; CARBOMER 940; ISOPROPYL MYRISTATE; BUTYLENE GLYCOL; TROLAMINE; WATER

PAMTEX COSMETIC Co., Ltd - WELLDERMA CLEAN HAND SANITIZER Gel

ACTIVE INGREDIENT

Alcohol

INACTIVE INGREDIENT

carbomer 940, butylene glycol, triethanolamine, polysorbate 60, isopropyl myristate, fragrance, water

PURPOSE

Hand sanitizer to help reduce bacteria that potentially can cause disease. For use when soap and water are not available.

keep out of reach of the children

INDICATIONS AND USAGE

Place enough product on hands to cover all surfaces. Rub hands together until dry.

Supervise children under 6 years of age when using this product to avoid swallowing.

WARNINGS

For external use only. Flammable. Keep away from heat or flame.

Do not use

- in children less than 2 months of age
- on open skin wounds

When using this product keep out of eyes, ears, and mouth. In case of contact with eyes, rinse thoroughly with water.

Stop use and ask a doctor if irritation or rash occurs. These may be signs of a serious condition.

Keep out of reach of children. If swallowed, get medical help or contact a Poison Control Center right away.

DOSAGE AND ADMINISTRATION

for external use only